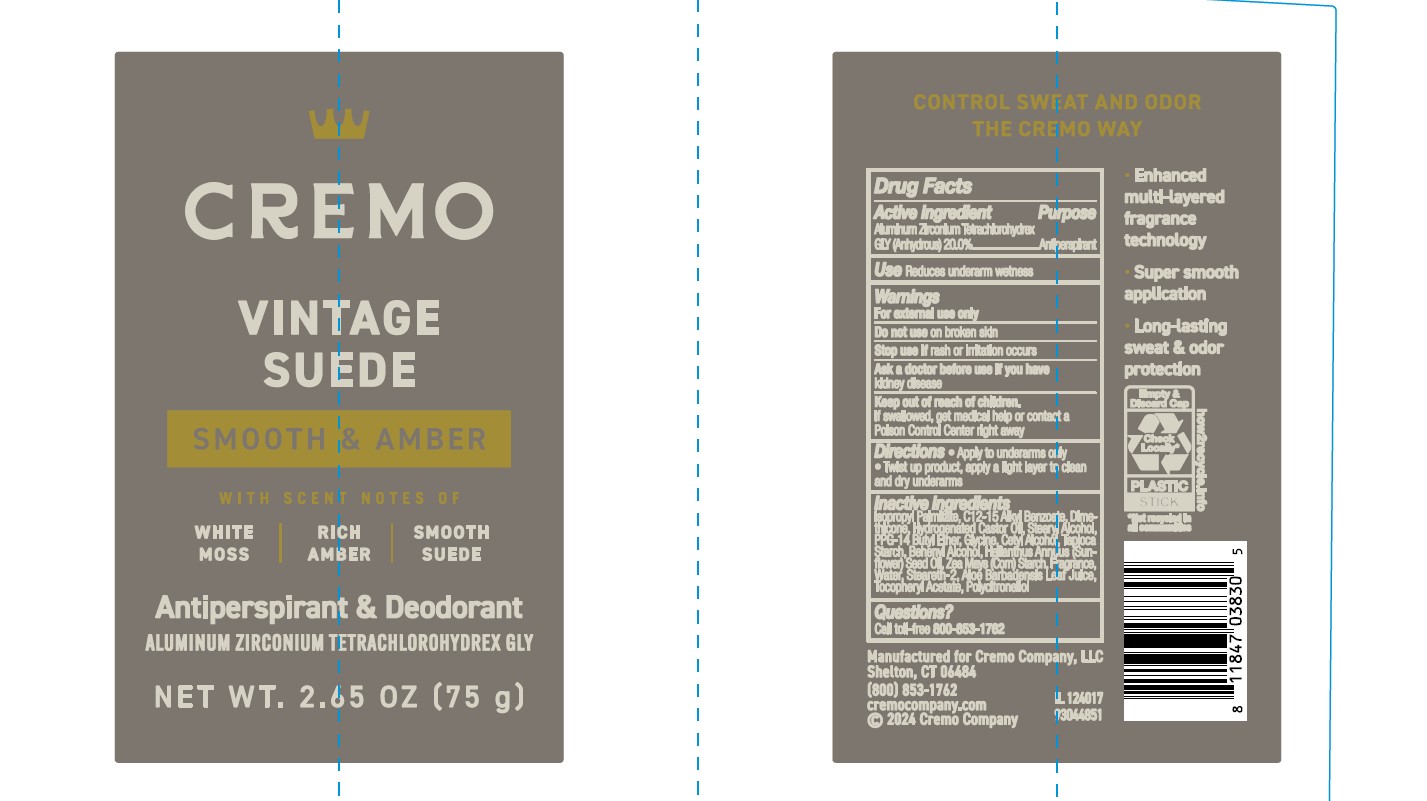 DRUG LABEL: Cremo Company
NDC: 71825-161 | Form: STICK
Manufacturer: Cremo Company
Category: otc | Type: HUMAN OTC DRUG LABEL
Date: 20241219

ACTIVE INGREDIENTS: ALUMINUM ZIRCONIUM TETRACHLOROHYDREX GLY 20 g/100 mL
INACTIVE INGREDIENTS: ALOE BARBADENSIS LEAF JUICE; HYDROGENATED CASTOR OIL; STEARYL ALCOHOL; HELIANTHUS ANNUUS (SUNFLOWER) SEED OIL; ISOPROPYL PALMITATE; GLYCINE; CETYL ALCOHOL; WATER; BEHENYL ALCOHOL; C12-15 ALKYL BENZOATE; PPG-14 BUTYL ETHER; TAPIOCA STARCH; STEARETH-2; .ALPHA.-TOCOPHEROL ACETATE; DIMETHICONE; ZEA MAYS (CORN) STARCH

Active Ingredient

Aluminum Zirconium Tetrachlorohydrex GLY (Anhydrous) (20.0%)

Purpose

Antiperspirant

Uses

Reduces underarm wetness

Warnings

For external use only

Do not use

on broken skin

Stop use if

rash or irritation occurs.

Ask a doctor before use if you have

kidney disease.

Keep out of reach of children.

If swallowed, get medical help or contact a Poison Control Center right away.

Directions

- Apply to underarms only
- Twist up product, apply a light layer to clean and dry underarms

Inactive ingredients

Isopropyl Palmitate, C12-15 Alkyl Benzoate, Dimethicone, Hydrogenated Castor Oil, Stearyl Alcohol, PPG-14 Butyl Ether, Glycine, Cetyl Alcohol, Tapioca Starch, Behenyl Alcohol, Helianthus Annuus (Sunflower) Seed Oil, Zea Mays (Corn) Starch, Fragrance, Water, Steareth-2, Aloe Barbadensis Leaf Juice, Tocopheryl Acetate, Polycitronellol.

Questions?

Call toll-free 800-853-1782

Primary Display Panel

Cremo
VINTAGE SUEDE
SMOOTH & AMBER
WITH SCENT NOTES OF
WHITE MOSS | RICH AMBER | SMOOTH SUEDE
Antiperspirant & Deodorant
ALUMINUM ZIRCONIUM TETRACHLOROHYDREX GLY
NET WT. 2.65 OZ (75 G)